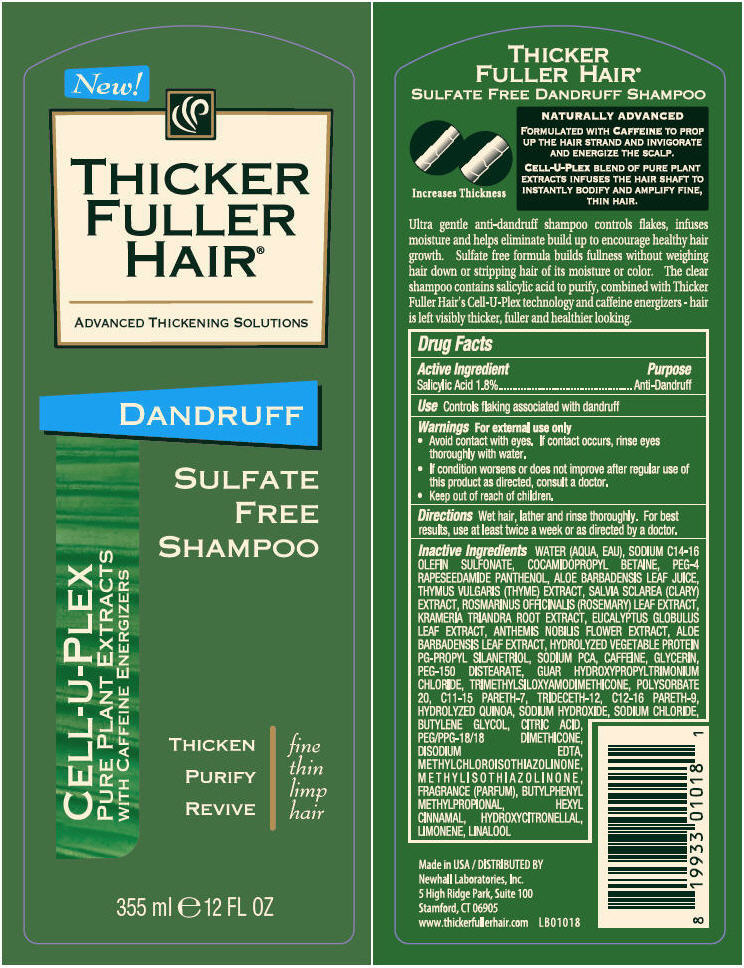 DRUG LABEL: Thicker Fuller Hair - Dandruff Sulfate Free
NDC: 31774-1018 | Form: SHAMPOO
Manufacturer: Golden Sun DBA Newhall Laboratories
Category: otc | Type: HUMAN OTC DRUG LABEL
Date: 20131202

ACTIVE INGREDIENTS: Salicylic Acid 18 mg/1 mL
INACTIVE INGREDIENTS: WATER; SODIUM C14-16 OLEFIN SULFONATE; COCAMIDOPROPYL BETAINE; PEG-4 RAPESEEDAMIDE; PANTHENOL; ALOE VERA LEAF; THYME; ROSEMARY; KRAMERIA LAPPACEA ROOT; EUCALYPTUS GLOBULUS LEAF; CHAMAEMELUM NOBILE FLOWER; SODIUM PYRROLIDONE CARBOXYLATE; CAFFEINE; GLYCERIN; PEG-150 DISTEARATE; POLYSORBATE 20; C11-15 PARETH-7; TRIDECETH-12; C12-16 PARETH-9; SODIUM HYDROXIDE; SODIUM CHLORIDE; BUTYLENE GLYCOL; CITRIC ACID MONOHYDRATE; PEG/PPG-18/18 DIMETHICONE; EDETATE DISODIUM; METHYLCHLOROISOTHIAZOLINONE; METHYLISOTHIAZOLINONE; BUTYLPHENYL METHYLPROPIONAL; .ALPHA.-HEXYLCINNAMALDEHYDE; HYDROXYCITRONELLAL; LINALOOL, (+/-)-

Thicker Fuller Hair® - Dandruff Sulfate Free

Drug Facts

Active Ingredient

Salicylic Acid 1.8%

Purpose

Anti-Dandruff

Use

Controls flaking associated with dandruff

Warnings

WHEN USING

For external use only

ASK DOCTOR

- Avoid contact with eyes. If contact occurs, rinse eyes thoroughly with water.

- If condition worsens or does not improve after regular use of this product as directed, consult a doctor.

- Keep out of reach of children.

Directions

Wet hair, lather and rinse thoroughly. For best results, use at least twice a week or as directed by a doctor.

Inactive Ingredients

WATER (AQUA, EAU), SODIUM C14-16 OLEFIN SULFONATE, COCAMIDOPROPYL BETAINE, PEG-4 RAPESEEDAMIDE PANTHENOL, ALOE BARBADENSIS LEAF JUICE, THYMUS VULGARIS (THYME) EXTRACT, SALVIA SCLAREA (CLARY) EXTRACT, ROSMARINUS OFFICINALIS (ROSEMARY) LEAF EXTRACT, KRAMERIA TRIANDRA ROOT EXTRACT, EUCALYPTUS GLOBULUS LEAF EXTRACT, ANTHEMIS NOBILIS FLOWER EXTRACT, ALOE BARBADENSIS LEAF EXTRACT, HYDROLYZED VEGETABLE PROTEIN PG-PROPYL SILANETRIOL, SODIUM PCA, CAFFEINE, GLYCERIN, PEG-150 DISTEARATE, GUAR HYDROXYPROPYLTRIMONIUM CHLORIDE, TRIMETHYLSILOXYAMODIMETHICONE, POLYSORBATE 20, C11-15 PARETH-7, TRIDECETH-12, C12-16 PARETH-9, HYDROLYZED QUINOA, SODIUM HYDROXIDE, SODIUM CHLORIDE, BUTYLENE GLYCOL, CITRIC ACID, PEG/PPG-18/18 DIMETHICONE, DISODIUM EDTA, METHYLCHLOROISOTHIAZOLINONE, METHYLISOTHIAZOLINONE, FRAGRANCE (PARFUM), BUTYLPHENYL METHYLPROPIONAL, HEXYL CINNAMAL, HYDROXYCITRONELLAL, LIMONENE, LINALOOL

DISTRIBUTED BY
Newhall Laboratories, Inc.
5 High Ridge Park, Suite 100
Stamford, CT 06905

PRINCIPAL DISPLAY PANEL - 355 ml Bottle Label

New!

THICKER
FULLER
HAIR®

ADVANCED THICKENING SOLUTIONS

DANDRUFF

SULFATE
FREE
SHAMPOO

CELL-U-PLEX
PURE PLANT EXTRACTS
WITH CAFFEINE ENERGIZERS

THICKEN
PURIFY
REVIVE
fine
thin
limp
hair

355 ml e 12 FL OZ